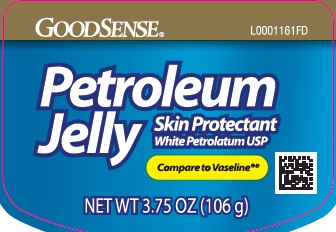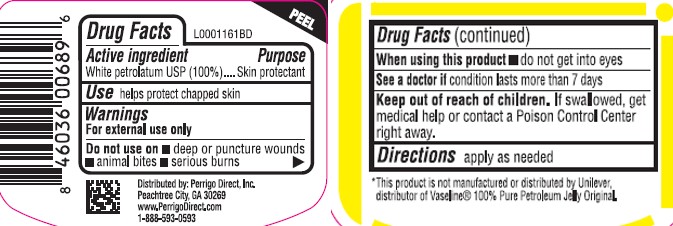 DRUG LABEL: Petroleum
NDC: 75981-069 | Form: JELLY
Manufacturer: Perrigo Direct, Inc
Category: otc | Type: HUMAN OTC DRUG LABEL
Date: 20260219

ACTIVE INGREDIENTS: PETROLATUM 1 g/1 g

Good Sense 069.001/069AA
Petroleum Jelly

Active ingredient

White Petrolatum USP (100%)

Purpose

Skin Protectant

Uses

helps protect chapped skin

Warnings

For external use only

Do not use on

- deep or puncture wounds
- animal bites
- serious burns

When using this product

- do not get into eyes

See a doctor if

condition lasts more than 7 days

Keep out of reach of children

If swallowed, get medical help or contact a Poison Control Center right away.

Directions

apply as needed

INACTIVE INGREDIENTS

NONE

ADVERSE REACTION

*This product is not manufactured or distributed by Unilever,

distributor of Vaseline® 100% Pure Petroleum Jelly Original.

Distributed by:Perrigo Direct, Inc

Peachtree City, GA 30269

www.PerrigoDirect.com

1-888-593-0593

principal display panel

GoodSense®

Petroleum Jelly

Skin Protectant

White Petrolatuem USP

Compare to Vaseline®*

NET WT 3.75 OZ (106 g)